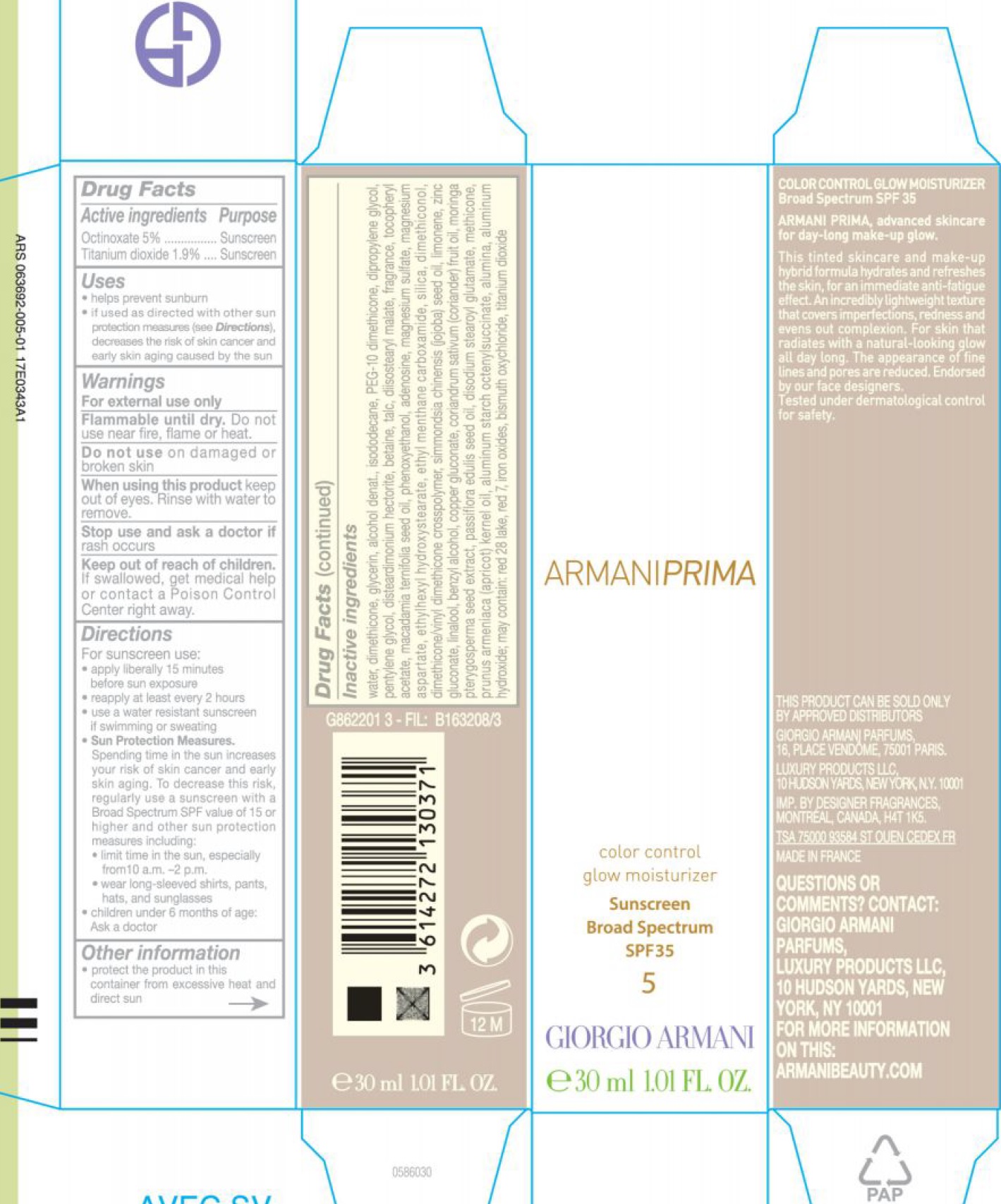 DRUG LABEL: 10 Armani Prima Control Glow Moisturizer SBS SPF 35
NDC: 70581-019 | Form: CREAM
Manufacturer: BPS 60
Category: otc | Type: HUMAN OTC DRUG LABEL
Date: 20231209

ACTIVE INGREDIENTS: OCTINOXATE 50 mg/1 mL; TITANIUM DIOXIDE 19 mg/1 mL
INACTIVE INGREDIENTS: WATER; DIMETHICONE; GLYCERIN; ALCOHOL; ISODODECANE; PEG-10 DIMETHICONE (600 CST); DIPROPYLENE GLYCOL; PENTYLENE GLYCOL; DISTEARDIMONIUM HECTORITE; BETAINE; TALC; DIISOSTEARYL MALATE; .ALPHA.-TOCOPHEROL ACETATE; MACADAMIA OIL; PHENOXYETHANOL; ADENOSINE; MAGNESIUM SULFATE, UNSPECIFIED FORM; MAGNESIUM ASPARTATE; ETHYLHEXYL HYDROXYSTEARATE; ETHYL MENTHANE CARBOXAMIDE; SILICON DIOXIDE; JOJOBA OIL; LIMONENE, (+)-; ZINC GLUCONATE; LINALOOL, (+/-)-; BENZYL ALCOHOL; COPPER GLUCONATE; CORIANDER OIL; MORINGA OLEIFERA SEED; PASSIFLORA EDULIS SEED OIL; DISODIUM STEAROYL GLUTAMATE; METHICONE (20 CST); APRICOT KERNEL OIL; ALUMINUM STARCH OCTENYLSUCCINATE; ALUMINUM OXIDE; ALUMINUM HYDROXIDE

10 Armani Prima Color Control Glow Moisturizer SBS SPF 35

Active ingredients

Octinoxate 5%

Titanium dioxide 1.9%

Purpose

Sunscreen

Uses

- helps prevent sunburn
- if used as directed with other sun protection measures (see decreases the risk of skin cancer and early skin aging caused by the sun Directions),

Warnings

For external use only

Do not use near fire, flame or heat. Flammable until dry.

Do not use

on damaged or broken skin

When using this product

keep out of eyes. Rinse with water to remove.

Stop use and ask a doctor if

rash occurs

Keep out of reach of children.

If swallowed, get medical help or contact a Poison Control Center right away.

Directions

For sunscreen use:

- apply liberally 15 minutes before sun exposure
- reapply at least every 2 hours
- use a water resistant sunscreen if swimming or sweating
- Spending time in the sun increases your risk of skin cancer and early skin aging. To decrease this risk, regularly use a sunscreen with a Broad Spectrum SPF value of 15 or higher and other sun protection measures including: Sun Protection Measures.
- limit time in the sun, especially from 10 a.m. -2 p.m.
- wear long-sleeved shirts, pants, hats, and sunglasses
- children under 6 months of age: Ask a doctor

Other information

- protect the product in this container from excessive heat and direct sun

Inactive ingredients

water, dimethicone, glycerin, alcohol denat., isododecane, PEG-10 dimethicone, dipropylene glycol, pentylene glycol, disteardimonium hectorite, betaine, talc, diisostearyl malate, fragrance, tocopheryl acetate, macadamia ternifolia seed oil, phenoxyethanol, adenosine, magnesium sulfate, magnesium aspartate, ethylhexyl hydroxystearate, ethyl menthane carboxamide, silica, dimethiconol, dimethicone/vinyl dimethoicone crosspolymer, simmondsia chinensis (jojoba) seed oil, limonene, zinc gluconate, linalool, benzyl alcohol, copper gluconate, coriandrum sativum (coriander) fruit oil, moringa pterygosperma seed extract, passiflora edulis seed oil, disodium stearoyl glutamate, methicone, prunus armeniaca (apricot) kernel oil, aluminum starch octenylsuccinate, alumina, aluminum hydroxide; may contain: red 28 lake, red 7, iron oxides, bismuth oxychloride, titanium dioxide